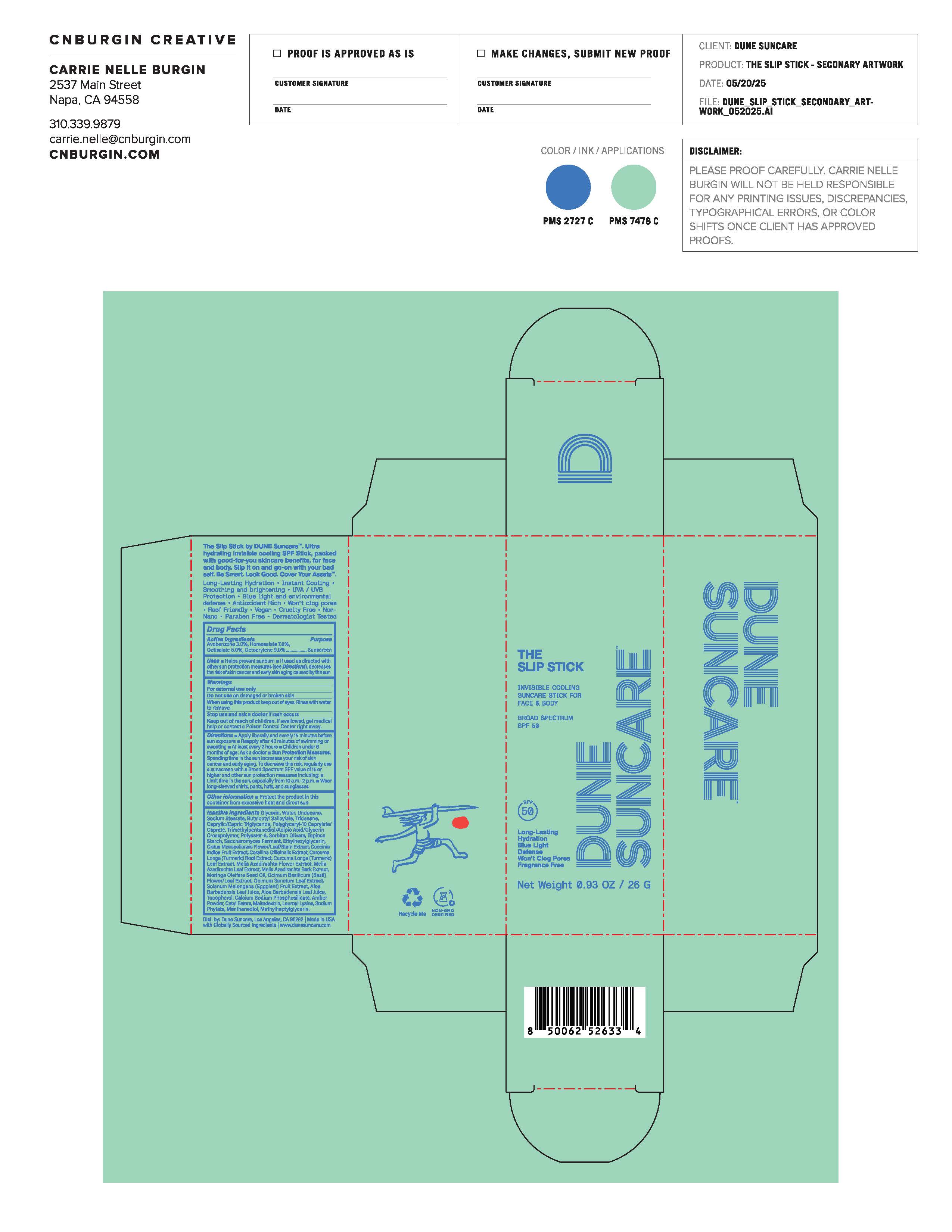 DRUG LABEL: THE SLIP
NDC: 82757-206 | Form: STICK
Manufacturer: Dune Suncare, Inc.
Category: otc | Type: HUMAN OTC DRUG LABEL
Date: 20251220

ACTIVE INGREDIENTS: AVOBENZONE 3 g/100 g; HOMOSALATE 7 g/100 g; OCTISALATE 5 g/100 g; OCTOCRYLENE 9 g/100 g
INACTIVE INGREDIENTS: CORALLINA OFFICINALIS; ETHYLHEXYLGLYCERIN; MELIA AZADIRACHTA LEAF; TRIMETHYLPENTANEDIOL/ADIPIC ACID/GLYCERIN CROSSPOLYMER (25000 MPA.S); COCCINIA GRANDIS FRUIT; CAPRYLIC/CAPRIC TRIGLYCERIDE; POLYESTER-8 (1400 MW, CYANODIPHENYLPROPENOYL CAPPED); CURCUMA LONGA LEAF; CALCIUM SODIUM PHOSPHOSILICATE; CURCUMA LONGA (TURMERIC) ROOT; .ALPHA.-TOCOPHEROL; CETYL ESTERS; LAUROYL LYSINE; SODIUM PHYTATE; SOLANUM MELONGENA WHOLE; SORBITAN OLIVATE; SACCHAROMYCES CEREVISIAE; POLYGLYCERYL-10 CAPRYLATE; AMBER POWDER; MELIA AZEDARACH BARK; OCIMUM AFRICANUM LEAF; ALOE BARBADENSIS LEAF JUICE; MALTODEXTRIN; GLYCERIN; METHYLENE GLYCOL; UNDECANE; WATER; SODIUM STEARATE; TRIDECANE; TAPIOCA STARCH; MORINGA OLEIFERA SEED OIL; OCIMUM BASILICUM FLOWERING TOP; CISTUS MONSPELIENSIS WHOLE; BUTYLOCTYL SALICYLATE

THE SLIP STICK

Active Ingredients

Avobenzone 3.0%

Homosalate 7.0%

Octisalate 5.0%

Octocrylene 9.0%

Purpose

Sunscreen

Uses

- Helps prevent sunburn
- If used as directed with other sun protection measures (see Directions), decreases the risk of skin cancer and early skin aging caused by the sun

Warnings

For external use only

Do not use

on damaged or broken skin

When using this product

keep out of eyes. Rinse with water to remove.

Stop use and ask a doctor

if rash occurs

Keep out of reach of children.

If swallowed, get medical help or contact a Poison Control Center right away.

Directions

- Apply liberally and evenly 15 minutes before sun exposure
- Reapply after 40 minutes of swimming or sweating
  - At least every 2 hours
  - Children under 6 months: Ask a doctor
- Sun Protection Measures.Spending time in the sun increases your risk of skin cancer and early aging. To decrease this risk, regularly use a sunscreen with Broad Spectrum SPF value of 15 or higher and other sun protection measures including:
- Limit time in the sun, especially from 10 a.m.–2 p.m.
- Wear long-sleeve shirts, pants, hats, and sunglasses

Other information

- protect the product in this container from excessive heat and direct sun

Inactive ingredients

Glycerin, Water, Undecane, Sodium Stearate, Butyloctyl Salicylate, Tridecane, Caprylic/Capric Triglyceride, Polyglyceryl-10 Caprylate/Caprate, Trimethylpentanediol/Adipic Acid/Glycerin Crosspolymer, Polyester-8, Sorbitan Olivate, Tapioca Starch, Saccharomyces Ferment, Ethylhexylglycerin, Cistus Monspeliensis Flower/Leaf/Stem Extract, Coccinia Indica Fruit Extract, Corallina Officinalis Extract, Curcuma Longa (Turmeric) Root Extract, Curcuma Longa (Turmeric) Leaf Extract, Melia Azadirachta Flower Extract, Melia Azadirachta Leaf Extract, Melia Azadirachta Bark Extract, Moringa Oleifera Seed Oil, Ocimum Basilicum (Basil) Flower/Leaf Extract, Ocimum Sanctum Leaf Extract, Solanum Melongena (Eggplant) Fruit Extract, Aloe Barbadensis Leaf Juice, Aloe Barbadensis Leaf Juice, Tocopherol, Calcium Sodium Phosphosilicate, Amber Powder, Cetyl Esters, Maltodextrin, Lauroyl Lysine, Sodium Phytate, Menthaneidiol, Methylheptylglycerin.

Principal Display Panel

DUNE SUNCARE

THE SLIP STICK

INVISIBLE COOLING

SUNCARE STICK FOR

FACE & BODY

BROAD SPECTRUM

SPF 50

Long-Lasting

Hydration

Blue Light

Defense

Won't Clog Pores

Fragrance Free

Net Weight 0.93 OZ / 26 g